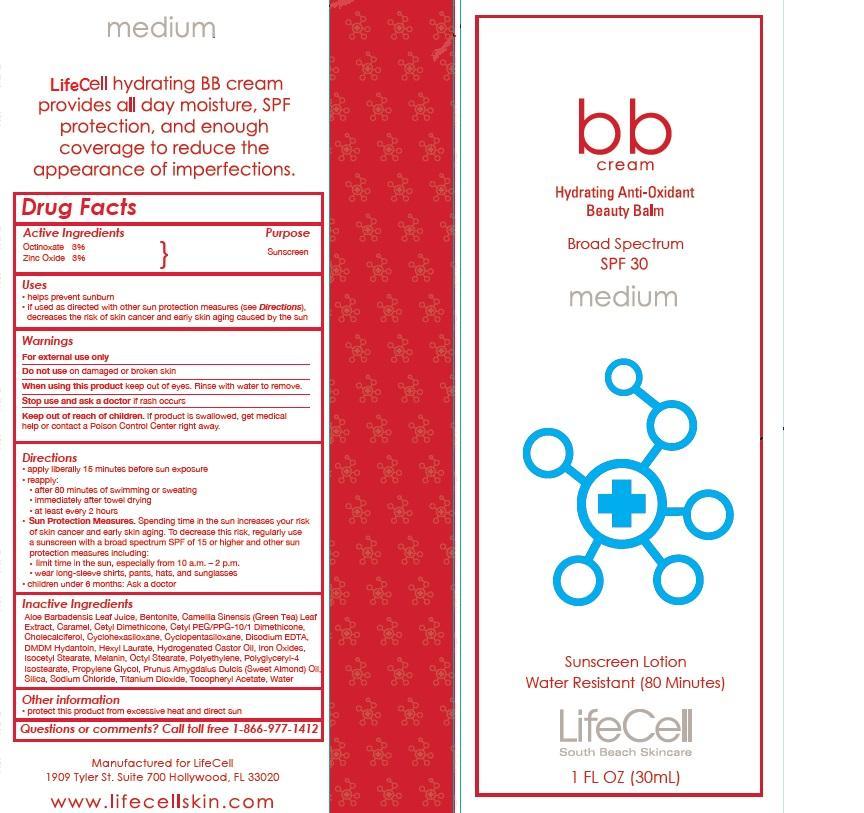 DRUG LABEL: LifeCell
NDC: 58443-0183 | Form: LOTION
Manufacturer: Prime Enterprises, Inc.
Category: otc | Type: HUMAN OTC DRUG LABEL
Date: 20200117

ACTIVE INGREDIENTS: OCTINOXATE 29.4 mg/1 mL; ZINC OXIDE 29.4 mg/1 mL
INACTIVE INGREDIENTS: ALOE VERA LEAF; BENTONITE; CARAMEL; CETYL DIMETHICONE 150; CETYL PEG/PPG-10/1 DIMETHICONE (HLB 2); CHOLECALCIFEROL; CYCLOMETHICONE 5; CYCLOMETHICONE 6; EDETATE DISODIUM; DMDM HYDANTOIN; HEXYL LAURATE; HYDROGENATED CASTOR OIL; FERRIC OXIDE RED; TRIETHOXYCAPRYLYLSILANE; ISOCETYL STEARATE; MELAMINE; OCTYL STEARATE; HIGH DENSITY POLYETHYLENE; POLYGLYCERYL-4 ISOSTEARATE; PROPYLENE GLYCOL; GREEN TEA LEAF; ALMOND OIL; SILICON DIOXIDE; SODIUM CHLORIDE; TITANIUM DIOXIDE; .ALPHA.-TOCOPHEROL ACETATE; WATER

Active ingredients

Octinoxate 3% and Zinc Oxide 3%

Purpose

Sunscreen

Uses

- helps prevent sunburn
- if used as directed with other sun protection measures (see Directions), decreases the risk of skin cancer and early skin aging caused by the sun

Warnings

OTHER SAFETY INFORMATION

For external use only

Do not use on damaged or broken skin

When using this product keep out of eyes. Rinse with water to remove.

Stop use and ask a doctor if rash occurs

Keep out of reach of children. If product is swallowed, get medical help or contact a Poison Control Center right away.

Directions

- apply liberally 15 minutes before sun exposure
- reapply:
- after 80 minutes of swimming or sweating
- immediately after towel drying
- at least every 2 hours
- Sun Protection Measures. Spending time in the sun increases your risk of skin cancer and early skin aging. To decrease this risk, regularly use a sunscreen with a broad spectrum SPF of 15 or higher and other sun protection measures including:
- limit time in the sun, especially from 10 a.m. - 2 p.m.
- wear long-sleeve shirts, pants, hats, and sunglasses
- children under 6 months: Ask a doctor.

Inactive Ingrediets:

Aloe Barbadensis Leaf Juice, Bentonite, Camellia Sinensis (Green Tea) Leaf Extract, Caramel, Cetyl Dimethicone, Cetyl PEG/PPG-10/1 Dimethicone, Cholecalciferol, Cyclohexasiloxane, Cyclopentasiloxane, Disodium EDTA, DMDM Hydantoin, Hexyl Laurate, Hydrogenated Castor Oil, Iron Oxides, Isocetyl Stearate, Melanin, Octyl Stearate, Polyethylene, Polyglyceryl-4 Isostearate, Propylene Glycol, Prunus Amygdalus Dulcis (Sweet Almond) Oil, Silica, Sodium Chloride, Titanium Dioxide, Tocopheryl Acetate, Water

Other information

- protect this product from excessive heat and direct sun

Questions or comments? Call toll free 1-866-977-1412

PRINCIPAL DISPLAY PANEL - 30mL Bottle Label

bb

cream

Hydrating Anti-Oxidant

Beauty Balm

Broad Spectrum

SPF 30

medium

Sunscreen Lotion

Water Resistant (80 Minutes)

LifeCell

South Beach Skincare

1 FL OZ (30mL)